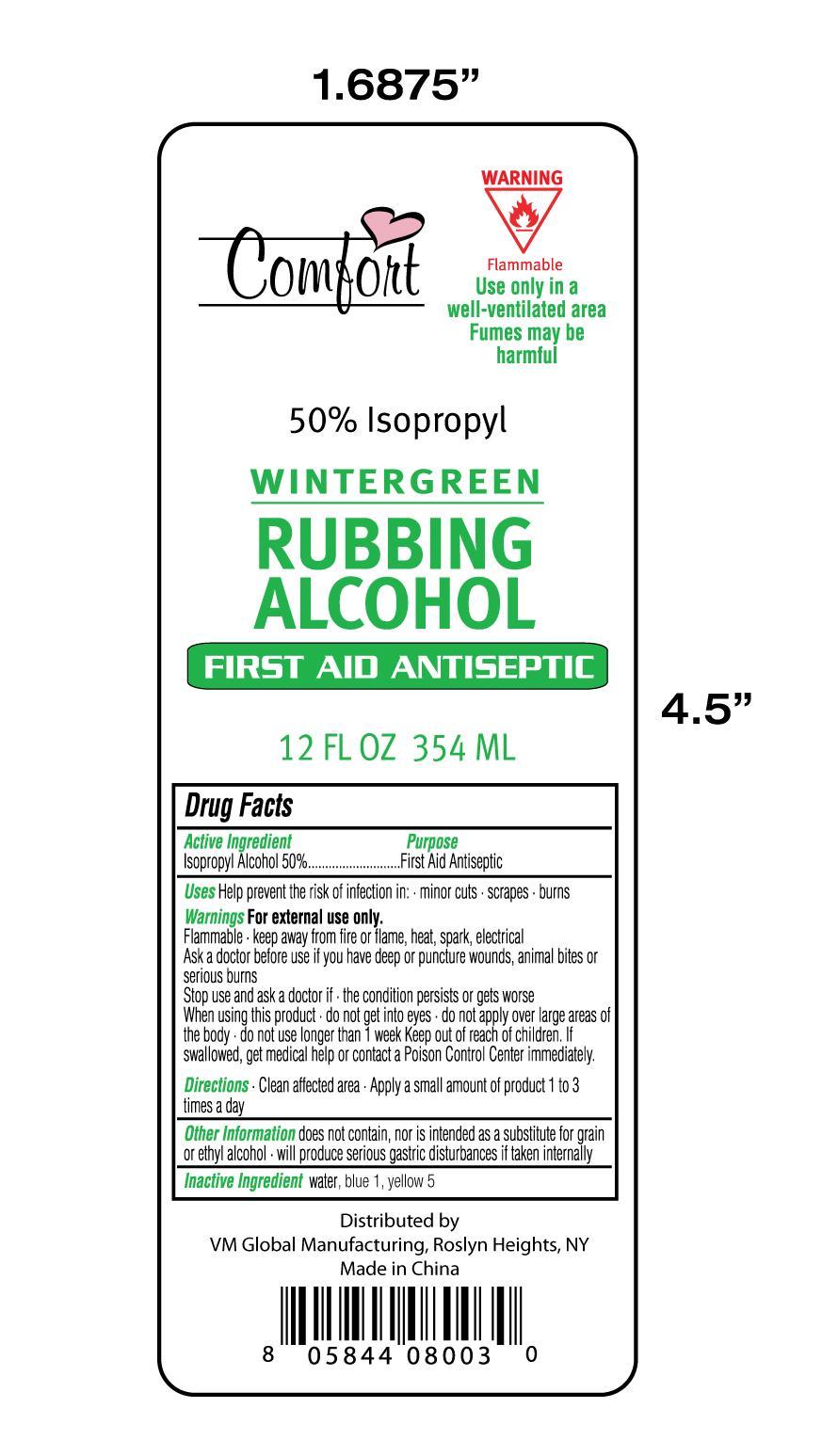 DRUG LABEL: Comfort
NDC: 50827-003 | Form: LIQUID
Manufacturer: WEIMEI Lianyungang Household Articles Manufacturing Co. LTD
Category: otc | Type: HUMAN OTC DRUG LABEL
Date: 20140128

ACTIVE INGREDIENTS: ISOPROPYL ALCOHOL 50 mL/100 mL
INACTIVE INGREDIENTS: Water; FD&C BLUE NO. 1; FD&C YELLOW NO. 5

Active Ingredient

Isopropyl Alcohol 50%

Purpose

First Aid Antiseptic

Uses

Help Prevent risk of infection in minor cuts, scrapes, burns

Warnings

For external use only

Flammable- keep away from fire or flame, heat, spark, electrical.

Ask a doctor before use if you have deep or punture wounds, animal bites or serious burns

Stop use and ask doctor if the condition persists or gets worse

When using this product, do not get into eyes, do not apply over large area of the body, do not use longer than 1 week

Keep out of reach of children

If swallowed, get medical help or contact a posion control center immediately

Directions

Clean affected area - apply a small amount of product 1 to 3 times a day

Other Information

does not container nor is intended as substitue for grain or ethyl alcohol, will produce serious gastric disturbances if taken internally

Inactive Ingredient

Water, Blue 1, yellow 5